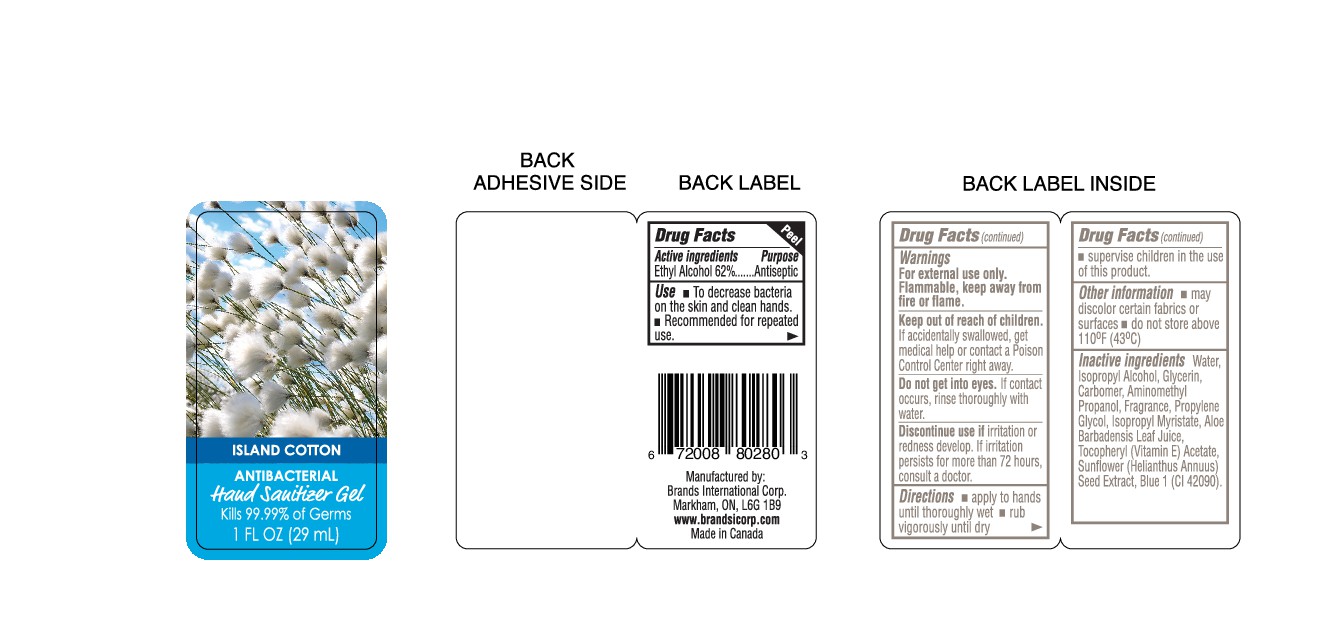 DRUG LABEL: Island Cotton
NDC: 50157-117 | Form: GEL
Manufacturer: Brands International Corp
Category: otc | Type: HUMAN OTC DRUG LABEL
Date: 20151102

ACTIVE INGREDIENTS: ALCOHOL 620 mL/1000 mL
INACTIVE INGREDIENTS: WATER; ISOPROPYL ALCOHOL; GLYCERIN; PROPYLENE GLYCOL; ISOPROPYL MYRISTATE; ALOE VERA LEAF; .ALPHA.-TOCOPHEROL ACETATE, DL-; FD&C BLUE NO. 1; CARBOMER 940; AMINOMETHYLPROPANOL; SUNFLOWER SEED

Active Ingredient - Ethyl Alcohol 62%

Purpose - Antiseptic

Use

To decrease bacteria on the skin and clean hands
Recommened for repeated use

Warnings

For external use only

Flammable, keep away from fire or flame

Keep out of reach of children

If accidently swallowed, get medical help or contact a Poison Control Center right away

SAFE HANDLING WARNING

Do not get into eyes

If contact occurs, rinse thoroughly with water

ASK DOCTOR

Discontinue use if irritation or redness develop. If irritation persists for more than 72 hours, consult a doctor

Directions

- apply to hands until thoroughly wet
- rub vigorously until dry
- supervise children in the use of this product

Other Information

- May discolour certain fabrics or surfaces
- do not store above 110 F (43 C)

INACTIVE INGREDIENT

Inactive Ingredients - Water, Isopropyl Alcohol, Glycerin, Carbomer, Aminomethyl Propanol, Fragrance, Propylene Glycol, Isopropyl Myristate, Aloe Barbadensis Leaf Juice, Tocopheryl (Vitamin E) Acetate, Sunflower (Helianthus Annulus) seed extract, Blue 1 (Cl 42090)